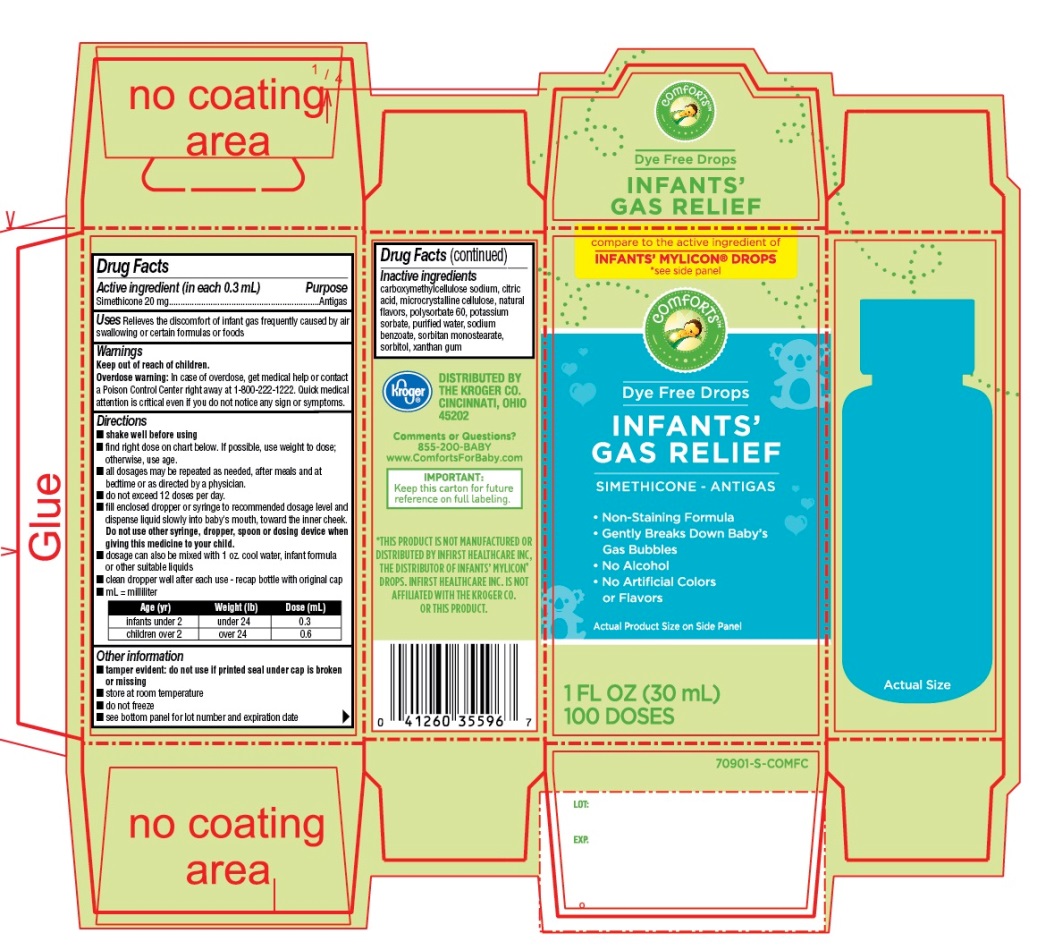 DRUG LABEL: Infants Gas Relief

NDC: 30142-171 | Form: EMULSION
Manufacturer: THE KROGER CO.
Category: otc | Type: HUMAN OTC DRUG LABEL
Date: 20250801

ACTIVE INGREDIENTS: DIMETHICONE, UNSPECIFIED 20 mg/0.3 mL
INACTIVE INGREDIENTS: CARBOXYMETHYLCELLULOSE SODIUM, UNSPECIFIED; ANHYDROUS CITRIC ACID; MICROCRYSTALLINE CELLULOSE; POLYSORBATE 60; POTASSIUM SORBATE; WATER; SODIUM BENZOATE; SORBITAN MONOSTEARATE; SORBITOL; XANTHAN GUM

Kroger INFANTSs GAS RELIEF Dye free DROPS

Active ingredient (in each 0.3 mL)

Simethicone 20 mg

Purpose

Antigas

Uses

Relieves the discomfort of infant gas frequently caused by air swallowing or certain formulas or foods

Directions

- shake well before using
- find right dose on chart below. If possible, use weight to dose; otherwise, use age.
- all dosages may be repeated as needed, after meals and at bedtime or as directed by a physician.
- do not exceed 12 doses per day.
- Fill enclosed dropper or syringe to recommended dosage level and dispense liquid slowly into baby’s mouth, toward the inner cheek. Do not use other syringe, dropper, spoon or dosing device when giving this medicine to your child.
- dosage can also be mixed with 1 oz. cool water, infant formula or other suitable liquids
- clean dropper well after each use-recap bottle with original cap
- mL = milliliter

Age (yr) | Weight (lb) | Dose (mL)
infants under 2 | under 24 | 0.3
children over 2 | over 24 | 0.6

Other information

- tamper evident: do not use if printed seal under cap is broken or missing
- store at room temperature
- do not freeze
- see bottom panel for lot number and expiration date

Inactive ingredients

carboxymethylcellulose sodium, citric acid, microcrystalline cellulose, natural flavors, polysorbate 60, potassium sorbate, purified water, sodium benzoate, sorbitan monostearate, sorbitol, xanthan gum

Comments or Questions?

855-200-BABY

www.ComfortsForBaby.com

Principal Display Panel

NDC# 30142-171-01

Dye Free Drops

INFANTS’ GAS RELIEF

*compare to the active ingredient of INFANTS’ MYLICON®DROPS

*see the side panel

Dye Free Drops

INFANTS’ GAS RELIEF

SIMETHICONE-ANTIGAS

- Non-Staining formula
- Gently Breaks Down Baby’s Gas Bubbles
- No alcohol
- No Artificial Colors or Flavor

1 Fl. OZ (30ml)

100 DOSES

IMPORTANT:Keep this carton for future reference on full labeling

DISTRIBUTED BY THE KROGER CO.

CINCINNATI, OHIO 45202

*THIS PRODUCT IS NOT MANUFACTURED OR DISTRIBUTED BY INFIRST HEALTHCARE INC., THE DISTRIBUTOR OF INFANTS’ MYLICON®DROPS. INFIRST HEALTHCARE INC. IS NOT AFFILIATED WITH THE KROGER CO. OR THIS PRODUCT.